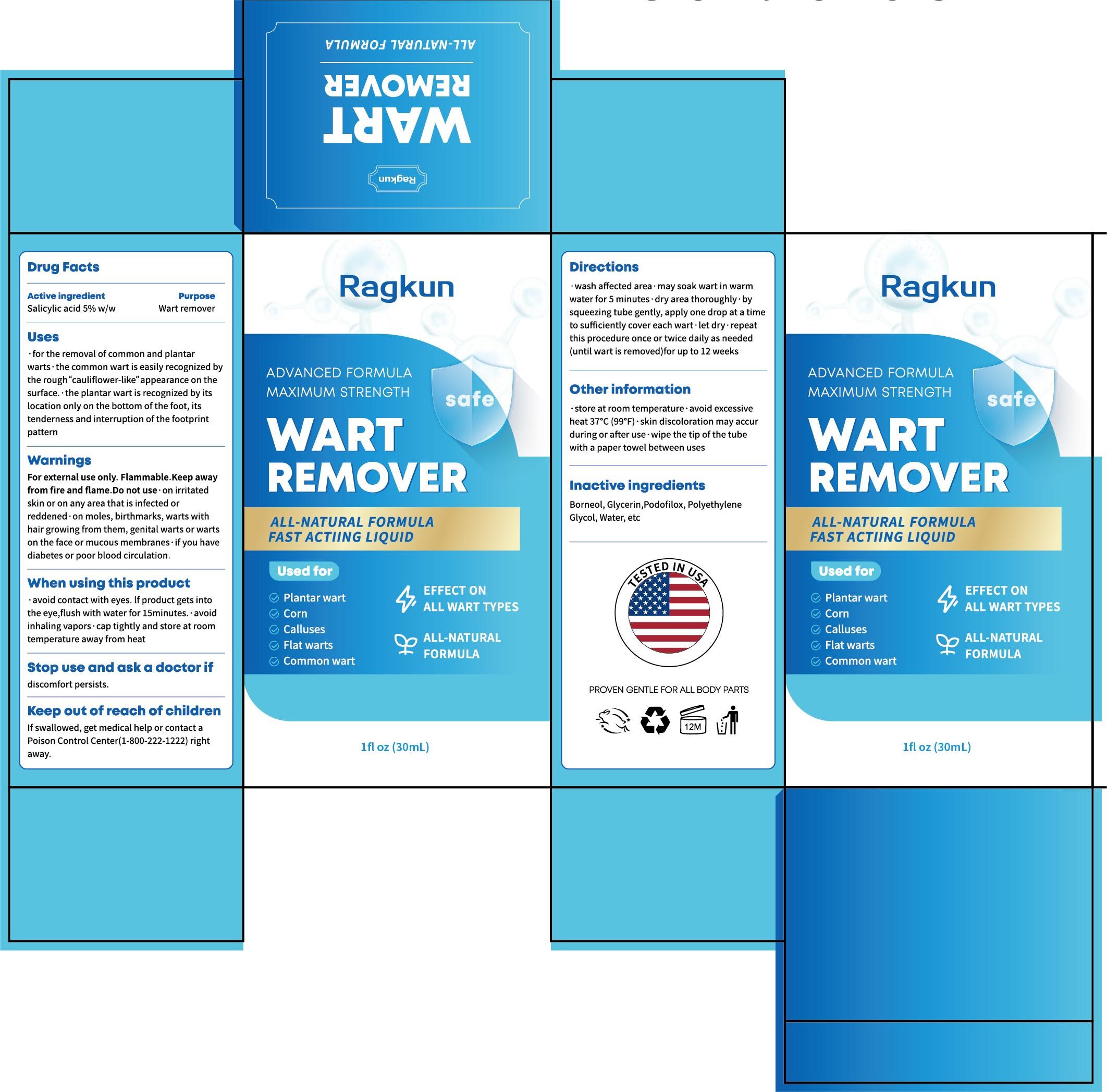 DRUG LABEL: Ragkun WART REMOVER
NDC: 84867-021 | Form: LIQUID
Manufacturer: Jiashen International Trading Co., Ltd.
Category: otc | Type: HUMAN OTC DRUG LABEL
Date: 20250820

ACTIVE INGREDIENTS: SALICYLIC ACID 5 g/100 mL
INACTIVE INGREDIENTS: POLYETHYLENE GLYCOL, UNSPECIFIED; BORNEOL; WATER; GLYCERIN; PODOFILOX

ACTIVE INGREDIENT

Salicylic acid 5%

INACTIVE INGREDIENT

Borneol

Glycerin

Podofilox

Water
Polyethylene Glycol

Keep out of Reach of children

PURPOSE

Plantar wart

Corn

Calluses

Flat warts
Common wart

Warnings
For external use only. Flammable.Keep awayfrom fire and flame.Do not use on irritatedskin or on any area that is infected orreddened·on moles, birthmarks, warts withhair growing from them, genital warts or wartson the face or mucous membranes*if you havediabetes or poor blood circulation.

INDICATIONS AND USAGE

avold contact wth eyes. f product gets intothe eye, ush with water for 15minutes. avoidinhalng vapors cap tighly and store at roomtemperature away from heat

DOSAGE AND ADMINISTRATION

wash affected area·may soak wart in warmwater for 5 minutes· dry area thoroughly· bysqueezing tube gently, apply one drop at a timeto sufficiently cover each wart·let dry·repeatthis procedure once or twice daily as needed(until wart is removed)for up to 12 weeks

OTHER SAFETY INFORMATION

store at room temperature*avoid excessiveheat 37°C (99°F)·skin discoloration may accurduring or after use· wipe the tip of the tubewith a paper towel between uses